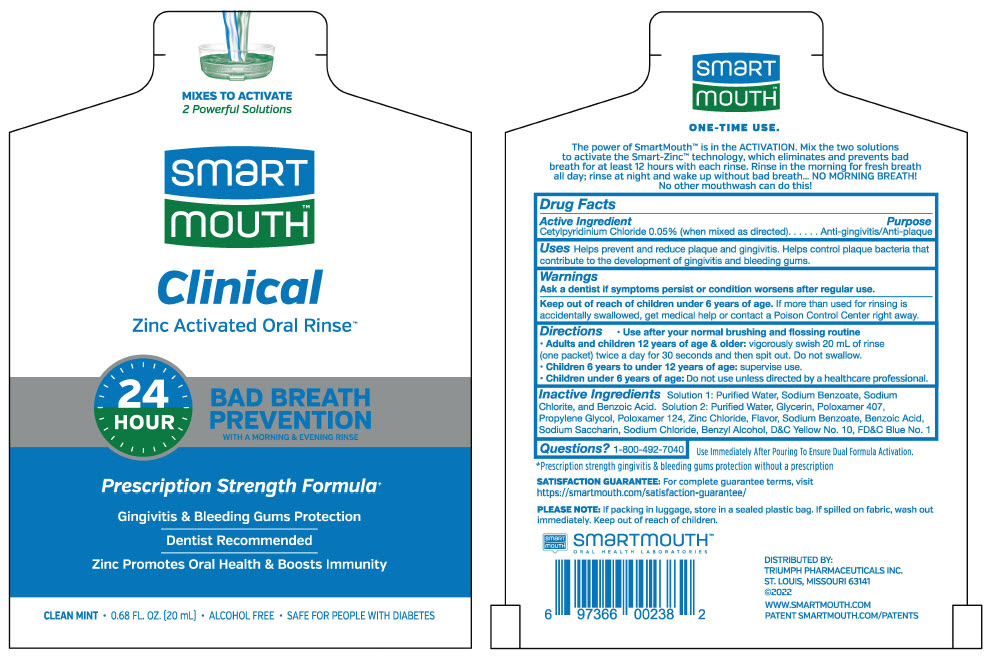 DRUG LABEL: SmartMouth Advance Clinical DDS Formula Mint
NDC: 76357-230 | Form: KIT | Route: DENTAL
Manufacturer: Triumph Pharmaceuticals, Inc.
Category: otc | Type: HUMAN OTC DRUG LABEL
Date: 20241212

ACTIVE INGREDIENTS: CETYLPYRIDINIUM CHLORIDE 500 mg/20 mL
INACTIVE INGREDIENTS: water; Sodium Benzoate; Benzoic Acid; Glycerin; Poloxamer 407; Propylene Glycol; Poloxamer 124; Zinc Chloride; Sodium; Saccharin Sodium; Sodium Chloride; Benzyl Alcohol

SmartMouth™ Advance Clinical DDS™ Formula Mint

DRUG FACTS

Active Ingredient

Cetylpyridinium Chloride 0.05% (when mixed as directed)

Purpose

Anti-gingivitis/Anti-plaque

Uses

Helps prevent and reduce plaque and gingivitis. Helps control plaque bacteria that contribute to the development of gingivitis and bleeding gums

Warnings

ASK DOCTOR

Ask a dentist if symptoms persist or condition worsens after regular use.

Keep out of reach of children under 6 years of age.

If more than used for rinsing is accidentally swallowed, get medical help or contact a Poison Control Center right away.

Directions

- Adults and children 12 years of age and older: vigorously swish 20 milliliters of rinse (one sample packet) twice a day for 30 seconds and then spit out. Do not swallow.
- Children 6 years to under 12 years of age: supervise use.
- Children under 6 years of age: do not use.

Other information

- This rinse is not intended to replace brushing or flossing.

Inactive Ingredients

Solution 1: Purified Water, Sodium Benzoate, Sodium Chlorite, and Benzoic Acid

Solution 2: Purified Water, Glycerin, Poloxamer 407, Propylene Glycol, Poloxamer 124, Zinc Chloride, Flavor, Sodium Benzoate, Benzoic Acid, Sodium Saccharin, Sodium Chloride, Benzyl Alcohol, D&C Yellow No. 10, FD&C Blue No. 1

Questions or comments

1-800-492-7040

SMARTMOUTH™ IS A TRADEMARK
OF AND DISTRIBUTED BY:
TRIUMPH PHARMACEUTICALS INC.
ST. LOUIS, MISSOURI 63141

PRINCIPAL DISPLAY PANEL - Kit Pouch

MIXES TO ACTIVATE
2 Powerful Solutions

smart
mouth™

Clinical
Zinc Activated Oral Rinse™

24
HOUR

BAD BREATH
PREVENTION
WITH A MORNING & EVENING RINSE

Prescription Strength Formula^+

Gingivitis & Bleeding Gums Protection

Dentist Recommended

Zinc Promotes Oral Health & Boosts Immunity

CLEAN MINT • 0.68 FL. OZ. [20 mL] • ALCOHOL FREE • SAFE FOR PEOPLE WITH DIABETES